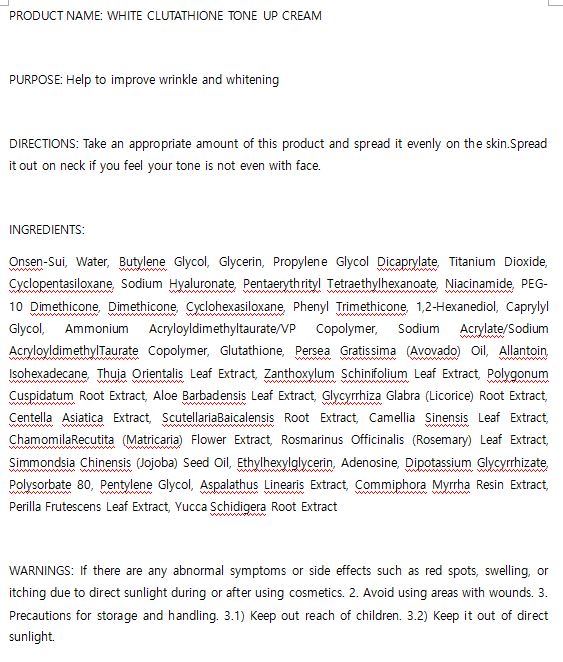 DRUG LABEL: W.SKIN WHITE GLUTATHIONE TONE UP
NDC: 74997-0012 | Form: CREAM
Manufacturer: J&J COMPANY
Category: otc | Type: HUMAN OTC DRUG LABEL
Date: 20210507

ACTIVE INGREDIENTS: NIACINAMIDE 2 g/100 mL
INACTIVE INGREDIENTS: GLYCERIN; WATER

J&J COMPANY - STOP-AGING PEPTIDE TONER

ACTIVE INGREDIENT

Niacinamide

INACTIVE INGREDIENT

Onsen-Sui, Water, Butylene Glycol, Glycerin, Propylene Glycol Dicaprylate, Titanium Dioxide, Cyclopentasiloxane, Sodium Hyaluronate, Pentaerythrityl Tetraethylhexanoate, Niacinamide, PEG-10 Dimethicone, Dimethicone, Cyclohexasiloxane, Phenyl Trimethicone, 1,2-Hexanediol, Caprylyl Glycol, Ammonium Acryloyldimethyltaurate/VP Copolymer, Sodium Acrylate/Sodium AcryloyldimethylTaurate Copolymer, Glutathione, Persea Gratissima (Avovado) Oil, Allantoin, Isohexadecane, Thuja Orientalis Leaf Extract, Zanthoxylum Schinifolium Leaf Extract, Polygonum Cuspidatum Root Extract, Aloe Barbadensis Leaf Extract, Glycyrrhiza Glabra (Licorice) Root Extract, Centella Asiatica Extract, ScutellariaBaicalensis Root Extract, Camellia Sinensis Leaf Extract, ChamomilaRecutita (Matricaria) Flower Extract, Rosmarinus Officinalis (Rosemary) Leaf Extract, Simmondsia Chinensis (Jojoba) Seed Oil, Ethylhexylglycerin, Adenosine, Dipotassium Glycyrrhizate, Polysorbate 80, Pentylene Glycol, Aspalathus Linearis Extract, Commiphora Myrrha Resin Extract, Perilla Frutescens Leaf Extract, Yucca Schidigera Root Extract

PURPOSE

Help to improve wrinkle and whitening

keep out of reach of the children

INDICATIONS AND USAGE

Take an appropriate amount of this product and spread it evenly on the skin.Spread it out on neck if you feel your tone is not even with face.

WARNINGS

If there are any abnormal symptoms or side effects such as red spots, swelling, or itching due to direct sunlight during or after using cosmetics. 2. Avoid using areas with wounds. 3. Precautions for storage and handling. 3.1) Keep out reach of children. 3.2) Keep it out of direct sunlight.

DOSAGE AND ADMINISTRATION

for external use only